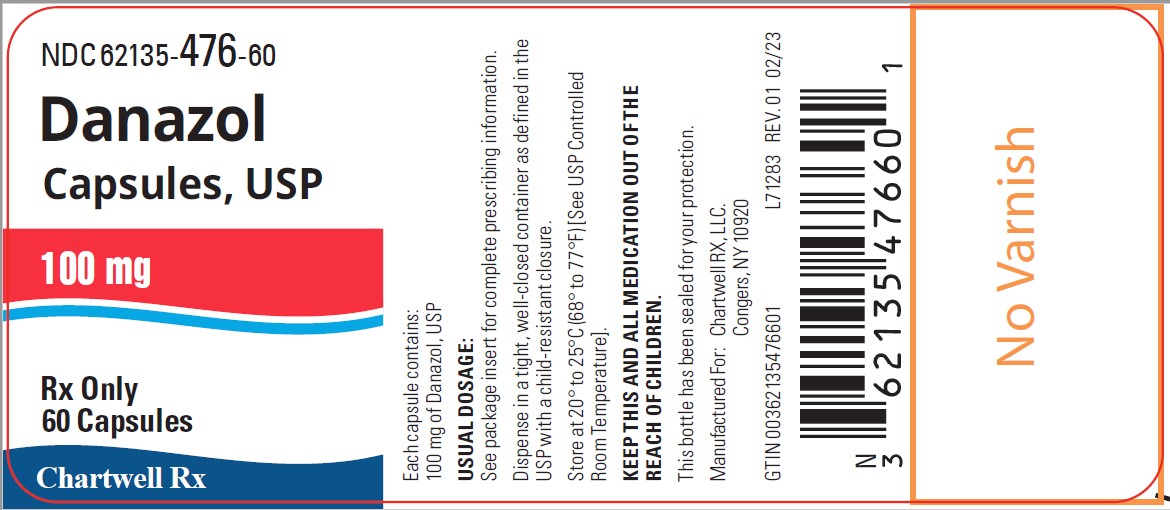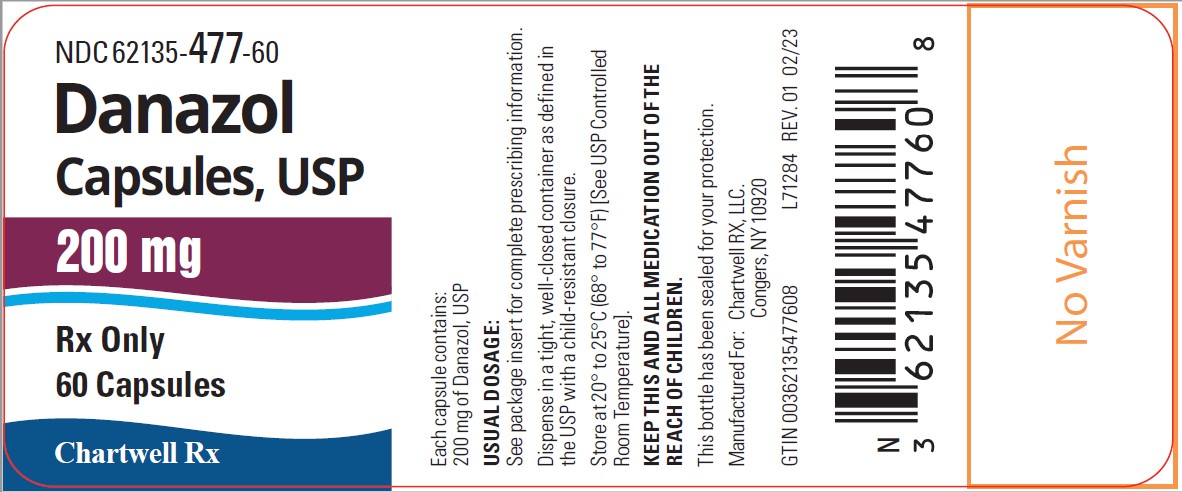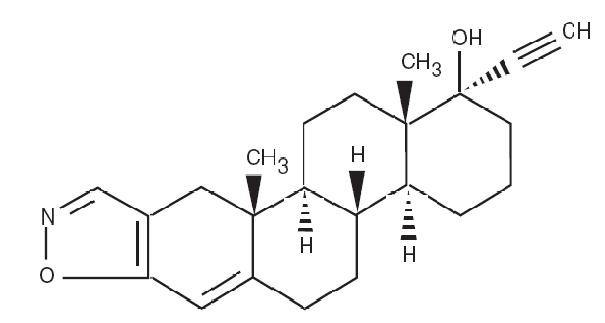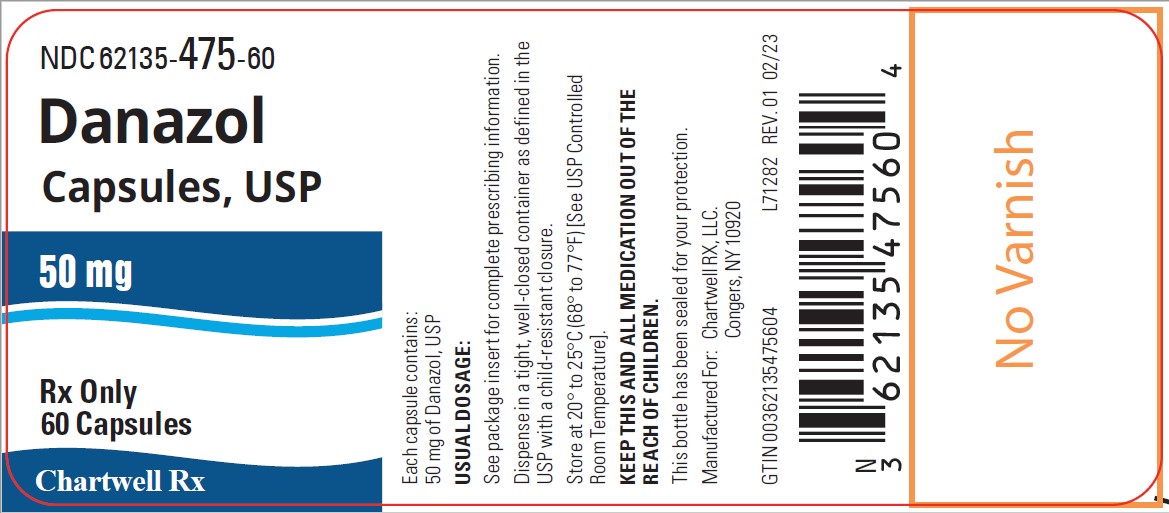 DRUG LABEL: Danazol
NDC: 62135-475 | Form: CAPSULE
Manufacturer: Chartwell RX, LLC.
Category: prescription | Type: HUMAN PRESCRIPTION DRUG LABEL
Date: 20241010

ACTIVE INGREDIENTS: DANAZOL 50 mg/1 1
INACTIVE INGREDIENTS: ANHYDROUS LACTOSE; LACTOSE MONOHYDRATE; MAGNESIUM STEARATE; STARCH, CORN; SODIUM LAURYL SULFATE; TALC; D&C YELLOW NO. 10; FD&C RED NO. 40; GELATIN; TITANIUM DIOXIDE; SHELLAC; ALCOHOL; FERROSOFERRIC OXIDE; BUTYL ALCOHOL; PROPYLENE GLYCOL; METHYL ALCOHOL; FD&C BLUE NO. 2; FD&C BLUE NO. 1; ALUMINUM OXIDE

Danazol Capsules, USP
Rx only

DESCRIPTION

Danazol is a synthetic steroid derived from ethisterone. It is a white to pale yellow crystalline powder, practically insoluble or insoluble in water, and sparingly soluble in alcohol. Chemically, danazol is 17α-Pregna-2,4-dien-20-yno [2,3- d]- isoxazol-17-ol. The molecular formula is C22H27NO2. It has a molecular weight of 337.46 and the following structural formula:

Danazol capsules for oral administration contain 50 mg, 100 mg or 200 mg danazol.

Inactive Ingredients: anhydrous lactose, lactose monohydrate, magnesium stearate, pregelatinized starch, sodium lauryl sulfate, talc. Capsule shells for 200 mg danazol contain D&C Yellow #10, FD&C Red #40, D&C Red #28, gelatin, and titanium dioxide. Capsule shells for 50 mg and 100 mg danazol contain D&C Yellow # 10, FD&C Red # 40, gelatin, and titanium dioxide. The capsule imprinting ink contains: shellac glaze in ethanol, iron oxide black, n-butyl alcohol, propylene glycol, ethanol, methanol, FD&C Blue No. 2 Aluminum Lake, FD&C Red No. 40 Aluminum Lake, FD&C Blue No. 1 Aluminum Lake, and D&C Yellow No. 10 Aluminum Lake.

CLINICAL PHARMACOLOGY

Danazol suppresses the pituitary-ovarian axis. This suppression is probably a combination of depressed hypothalamic-pituitary response to lowered estrogen production, the alteration of sex steroid metabolism, and interaction of danazol with sex hormone receptors. The only other demonstrable hormonal effect is weak androgenic activity. Danazol depresses the output of both follicle-stimulating hormone (FSH) and luteinizing hormone (LH).

Recent evidence suggests a direct inhibitory effect at gonadal sites and a binding of danazol to receptors of gonadal steroids at target organs. In addition, danazol has been shown to significantly decrease IgG, IgM and IgA levels, as well as phospholipid and IgG isotope autoantibodies in patients with endometriosis and associated elevations of autoantibodies, suggesting this could be another mechanism by which it facilitates regression of the disease.

In the treatment of endometriosis, danazol alters the normal and ectopic endometrial tissue so that it becomes inactive and atrophic. Complete resolution of endometrial lesions occurs in the majority of cases.

Changes in vaginal cytology and cervical mucus reflect the suppressive effect of danazol on the pituitary-ovarian axis.

Changes in the menstrual pattern may occur.

Generally, the pituitary-suppressive action of danazol is reversible. Ovulation and cyclic bleeding usually return within 60 to 90 days when therapy with danazol is discontinued.

In the treatment of hereditary angioedema, danazol at effective doses prevents attacks of the disease characterized by episodic edema of the abdominal viscera, extremities, face, and airway which may be disabling and, if the airway is involved, fatal. In addition, danazol corrects partially or completely the primary biochemical abnormality of hereditary angioedema by increasing the levels of the deficient C1 esterase inhibitor (C1EI). As a result of this action the serum levels of the C4 component of the complement system are also increased.

Pharmacokinetics

Absorption: After oral administration of a 400 mg dose to healthy male volunteers, peak plasma concentrations of danazol are reached between 2 and 8 hours, with a median Tmax value of 4 hours. Steady state conditions are observed following 6 days of twice daily dosing of danazol capsules.

The pharmacokinetic parameters for danazol capsules after administering a 400 mg oral dose to healthy males are summarized in the following table:

Parameters | Mean ± SD (n=15)
Cmax (ng/mL) | 69.6 ± 29.9
Tmax (h) | 2.47 ± 1.62
AUC0-∞ (ng*h/mL) | 601 ± 181
t1/2 (h) | 9.70 ± 3.29
Total Body Clearance (L/h) | 727 ± 221

The pharmacokinetic parameters for danazol capsules after oral administration of 100, 200 and 400 mg single doses to healthy female volunteers are summarized in the following table:

Dose (mg) | Mean Cmax ± SD (ng/mL) |  | Mean Tmax (h) |  | Mean AUC0-∞ ± SD (ng*h/mL)
 | Fasting | Fed | Fasting | Fed | Fasting | Fed
100 | 45.9 ± 23.9 | 113.8 ± 46.0 | 1-8 | 2-6 | 484 ± 263 | 741 ± 265
200 | 63.8 ± 27.7 | 159 ± 57.3 | 1-6 | 2-4 | 681 ± 363 | 1252 ± 307
400 | 60.4 ± 30.0 | 253.7 ± 105.5 | 1-6 | 2-4 | 754 ± 443 | 1851 ± 605

Dose proportionality: Bioavailability studies indicate that blood levels do not increase proportionally with increases in the administered dose.

Single dose administration of danazol capsules in healthy female volunteers found that a 4-fold increase in dose produced only a 1.6 and 2.5-fold increase in AUC and a 1.3 and 2.2-fold increase in Cmax in the fasted and fed state, respectively. A similar degree of non-dose proportionality was observed at steady state.

Food Effect: Single dose administration of 100 mg and 200 mg capsules of danazol to female volunteers showed that both the extent of availability and the maximum plasma concentration increased by 3 to 4 fold, respectively, following a meal (> 30 grams of fat), when compared to the fasted state. Further, food also delayed mean time to peak concentration of danazol by about 30 minutes. Even after multiple dosing under less extreme food/fasting conditions, there remained approximately a 2 to 2.5 fold difference in bioavailability between the fed and fasted states.

Distribution: Danazol is lipophilic and can partition into cell membranes, indicating the likelihood of distribution into deep tissue compartments.

Metabolism and Excretion: Danazol appears to be metabolized and the metabolites are eliminated by renal and fecal pathways. The two primary metabolites excreted in the urine are 2-hydroxymethyl danazol and ethisterone. At least ten different products were identified in feces.

The reported elimination half-life of danazol is variable across studies. The mean half-life of danazol in healthy males is 9.7 h. After 6 months of 200 mg three times a day dosing in endometriosis patients, the half-life of danazol was reported as 23.7 hours.

INDICATIONS AND USAGE

Endometriosis. Danazol capsules are indicated for the treatment of endometriosis amenable to hormonal management.

Hereditary Angioedema. Danazol capsules are indicated for the prevention of attacks of angioedema of all types (cutaneous, abdominal, laryngeal) in males and females.

CONTRAINDICATIONS

Danazol capsules should not be administered to patients with:

1. Undiagnosed abnormal genital bleeding.
2. Markedly impaired hepatic, renal, or cardiac function.
3. Pregnancy (see WARNINGS).
4. Breast feeding.
5. Porphyria-Danazol capsules can induce ALA synthetase activity and hence porphyrin metabolism.
6. Androgen-dependent tumor.
7. Active thrombosis or thromboembolic disease and history of such events.
8. Hypersensitivity to danazol.

WARNINGS

Use of danazol in pregnancy is contraindicated. A sensitive test (e.g., beta subunit test if available) capable of determining early pregnancy is recommended immediately prior to start of therapy. Additionally a non-hormonal method of contraception should be used during therapy. If a patient becomes pregnant while taking danazol, administration of the drug should be discontinued and the patient should be apprised of the potential risk to the fetus. Exposure to danazol in utero may result in androgenic effects on the female fetus; reports of clitoral hypertrophy, labial fusion, urogenital sinus defect, vaginal atresia, and ambiguous genitalia have been received (see PRECAUTIONS: Pregnancy, Teratogenic Effects).

Thromboembolism, thrombotic and thrombophlebitic events including sagittal sinus thrombosis and life-threatening or fatal strokes have been reported.

Experience with long-term therapy with danazol is limited. Peliosis hepatis and benign hepatic adenoma have been observed with long-term use. Peliosis hepatis and hepatic adenoma may be silent until complicated by acute, potentially life-threatening intraabdominal hemorrhage. The physician therefore should be alert to this possibility. Attempts should be made to determine the lowest dose that will provide adequate protection. If the drug was begun at a time of exacerbation of hereditary angioneurotic edema due to trauma, stress or other cause, periodic attempts to decrease or withdraw therapy should be considered.

Danazol has been associated with several cases of benign intracranial hypertension also known as pseudotumor cerebri. Early signs and symptoms of benign intracranial hypertension include papilledema, headache, nausea and vomiting, and visual disturbances. Patients with these symptoms should be screened for papilledema and, if present, the patients should be advised to discontinue danazol immediately and be referred to a neurologist for further diagnosis and care.

A temporary alteration of lipoproteins in the form of decreased high density lipoproteins and possibly increased low density lipoproteins has been reported during danazol therapy. These alterations may be marked, and prescribers should consider the potential impact on the risk of atherosclerosis and coronary artery disease in accordance with the potential benefit of the therapy to the patient.

Patients should be watched closely for signs of androgenic effects some of which may not be reversible even when drug administration is stopped.

PRECAUTIONS

Because danazol capsules may cause some degree of fluid retention, conditions that might be influenced by this factor, such as epilepsy, migraine, or cardiac or renal dysfunction, polycythemia and hypertension require careful observation. Use with caution in patients with diabetes mellitus.

Since hepatic dysfunction manifested by modest increases in serum transaminases levels has been reported in patients treated with danazol capsules, periodic liver function tests should be performed (see WARNINGS and ADVERSE REACTIONS).

Administration of danazol has been reported to cause exacerbation of the manifestations of acute intermittent porphyria (see CONTRAINDICATIONS).

Laboratory monitoring of the hematologic state should be considered.

Drug Interactions:

Prolongation of prothrombin time occurs in patients stabilized on warfarin.

Therapy with danazol may cause an increase in carbamazepine levels in patients taking both drugs.

Danazol can cause insulin resistance. Caution should be exercised when used with antidiabetic drugs.

Danazol may raise the plasma levels of cyclosporin and tacrolimus, leading to an increase of the renal toxicity of these drugs. Monitoring of systemic concentrations of these drugs and appropriate dose adjustments may be needed when used concomitantly with danazol.

Danazol can increase the calcemic response to synthetic vitamin D analogs in primary hypoparathyroidism.

The risk of myopathy and rhabdomyolysis is increased by concomitant administration of danazol with statins such as simvastatin, atorvastatin and lovastatin. Caution should be exercised if used concomitantly. Consult the product labeling for statin drugs for specific information on dose restrictions in presence of danazol.

Laboratory Tests:

Danazol treatment may interfere with laboratory determinations of testosterone, androstenedione and dehydroepiandrosterone. Other metabolic events include a reduction in thyroid binding globulin and T4 with increased uptake of T3, but without disturbance of thyroid stimulating hormone or of free thyroxin index.

Carcinogenesis, Mutagenesis, Impairment of Fertility:

Current data are insufficient to assess the carcinogenicity of danazol.

Pregnancy, Teratogenic Effects:

(See CONTRAINDICATIONS.) Danazol administered orally to pregnant rats from the 6th through the 15th day of gestation at doses up to 250 mg/kg/day (7-15 times the human dose) did not result in drug-induced embryotoxicity or teratogenicity, nor difference in litter size, viability or weight of offspring compared to controls. In rabbits, the administration of danazol on days 6-18 of gestation at doses of 60 mg/kg/day and above (2-4 times the human dose) resulted in inhibition of fetal development.

Nursing Mothers: (See CONTRAINDICATIONS.)

Pediatric Use: Safety and effectiveness in pediatric patients have not been established.

Geriatric Use: Clinical studies of danazol capsules did not include sufficient numbers of subjects aged 65 and over to determine the safety and effectiveness of Danocrine in elderly patients.

ADVERSE REACTIONS

The following events have been reported in association with the use of danazol capsules:

Androgen like effects include weight gain, acne and seborrhea. Mild hirsutism, edema, hair loss, voice change, which may take the form of hoarseness, sore throat or of instability or deepening of pitch, may occur and may persist after cessation of therapy. Hypertrophy of the clitoris is rare.

Other possible endocrine effects are menstrual disturbances including spotting, alteration of the timing of the cycle and amenorrhea. Although cyclical bleeding and ovulation usually return within 60-90 days after discontinuation of therapy with danazol capsules, persistent amenorrhea has occasionally been reported.

Flushing, sweating, vaginal dryness and irritation and reduction in breast size, may reflect lowering of estrogen. Nervousness and emotional lability have been reported. In the male a modest reduction in spermatogenesis may be evident during treatment. Abnormalities in semen volume, viscosity, sperm count, and motility may occur in patients receiving long-term therapy.

Hepatic dysfunction, as evidenced by reversible elevated serum enzymes and/or jaundice, has been reported in patients receiving a daily dosage of danazol capsules of 400 mg or more. It is recommended that patients receiving danazol capsules be monitored for hepatic dysfunction by laboratory tests and clinical observation. Serious hepatic toxicity including cholestatic jaundice, peliosis hepatis, hepatic adenoma, hepatocellular injury, hepatocellular jaundice and hepatic failure have been reported (see WARNINGS and PRECAUTIONS).

Abnormalities in laboratory tests may occur during therapy with danazol capsules including CPK, glucose tolerance, glucagon, thyroid binding globulin, sex hormone binding globulin, other plasma proteins, lipids and lipoproteins.

The following reactions have been reported, a causal relationship to the administration of danazol capsules has neither been confirmed nor refuted; allergic: urticaria, pruritus and rarely, nasal congestion; CNS effects: headache, nervousness and emotional lability, dizziness and fainting, depression, fatigue, sleep disorders, tremor, paresthesias, weakness, visual disturbances, and rarely, benign intracranial hypertension, anxiety, changes in appetite, chills, and rarely convulsions, Guillain-Barre syndrome; gastrointestinal: gastroenteritis, nausea, vomiting, constipation, and rarely, pancreatitis and splenic peliosis; musculoskeletal: muscle cramps or spasms, or pains, joint pain, joint lockup, joint swelling, pain in back, neck, or extremities, and rarely, carpal tunnel syndrome which may be secondary to fluid retention; genitourinary: hematuria, prolonged posttherapy amenorrhea; hematologic: an increase in red cell and platelet count. Reversible erythrocytosis, leukocytosis or polycythemia may be provoked. Eosinophilia, leukopenia and thrombocytopenia have also been noted. Skin: rashes (maculopapular, vesicular, papular, purpuric, petechial), and rarely, sun sensitivity, Stevens-Johnson syndrome and erythema multiforme; other: increased insulin requirements in diabetic patients, change in libido, myocardial infarction, palpitation, tachycardia, elevation in blood pressure, interstitial pneumonitis, and rarely, cataracts, bleeding gums, fever, pelvic pain, nipple discharge. Malignant liver tumors have been reported in rare instances, after long-term use.

DOSAGE AND ADMINISTRATION

Endometriosis. In moderate to severe disease, or in patients infertile due to endometriosis, a starting dose of 800 mg given in two divided doses is recommended. Amenorrhea and rapid response to painful symptoms is best achieved at this dosage level. Gradual downward titration to a dose sufficient to maintain amenorrhea may be considered depending upon patient response. For mild cases, an initial daily dose of 200 mg to 400 mg given in two divided doses is recommended and may be adjusted depending on patient response. Therapy should begin during menstruation. Otherwise, appropriate tests should be performed to ensure that the patient is not pregnant while on therapy with danazol capsules (see CONTRAINDICATIONS and WARNINGS). It is essential that therapy continue uninterrupted for 3 to 6 months but may be extended to 9 months if necessary. After termination of therapy, if symptoms recur, treatment can be reinstituted.

Hereditary Angioedema. The dosage requirements for continuous treatment of hereditary angioedema with danazol capsules should be individualized on the basis of the clinical response of the patient. It is recommended that the patient be started on 200 mg, two or three times a day. After a favorable initial response is obtained in terms of prevention of episodes of edematous attacks, the proper continuing dosage should be determined by decreasing the dosage by 50% or less at intervals of one to three months or longer if frequency of attacks prior to treatment dictates. If an attack occurs, the daily dosage may be increased by up to 200 mg. During the dose adjusting phase, close monitoring of the patient's response is indicated, particularly if the patient has a history of airway involvement.

HOW SUPPLIED

Danazol Capsules USP, 50 mg are available as maize opaque/white opaque capsules imprinted with logo "LANNETT" on the cap and "1392" on the body and are supplied in:

Bottles of 60 (NDC 62135-475-60)

Danazol Capsules USP, 100 mg are available as maize opaque/maize opaque capsules imprinted with logo "LANNETT" on the cap and "1368" on the body and are supplied in:

Bottles of 60 (NDC 62135-476-60)

Danazol Capsules USP, 200 mg are available as orange opaque/orange opaque capsules imprinted with logo "LANNETT" on the cap and "1369" on the body and are supplied in:

Bottles of 60 (NDC 62135-477-60)

Store at 20° to 25°C (68° to 77°F) [see USP Controlled Room Temperature].

Dispense in a well-closed container with a child-resistant closure as defined in the USP.

Manufactured for:
Chartwell RX, LLC.
Congers, NY 10920

L71285

Rev. 02/2023

PACKAGE LABEL.PRINCIPAL DISPLAY PANEL

Danazol Capsules USP, 50 mg- NDC 62135-475-60 -60's bottle label

Danazol Capsules USP, 100 mg- NDC 62135-476-60 -60's bottle label

Danazol Capsules USP, 200 mg- NDC 62135-477-60 -60's bottle label